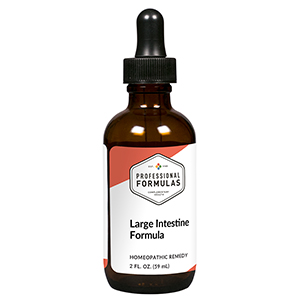 DRUG LABEL: Large Intestine Formula
NDC: 63083-2103 | Form: LIQUID
Manufacturer: Professional Complementary Health Formulas
Category: homeopathic | Type: HUMAN OTC DRUG LABEL
Date: 20190815

ACTIVE INGREDIENTS: SCLEROMITRION DIFFUSUM WHOLE 1 [hp_X]/59 mL; FERROSOFERRIC OXIDE 1 [hp_X]/59 mL; SANGUISORBA OFFICINALIS ROOT 1 [hp_X]/59 mL; MAGNOLIA OFFICINALIS BARK 1 [hp_X]/59 mL; STYPHNOLOBIUM JAPONICUM FLOWER 1 [hp_X]/59 mL; SCUTELLARIA BAICALENSIS ROOT 1 [hp_X]/59 mL; LONICERA HYPOGLAUCA FLOWER 1 [hp_X]/59 mL; TARAXACUM SINICUM WHOLE 1 [hp_X]/59 mL; ANGELICA GIGAS ROOT 3 [hp_X]/59 mL
INACTIVE INGREDIENTS: ALCOHOL; WATER

C103

ACTIVE INGREDIENTS

Bai-Hua-She-She-Cao 1X
Chih-Shih 1X
Di-Yu 1X
Hou-Pu 1X
Huai-Hua 1X
Huang-Qin 1X
Jin-Yin-Hua 1X
Pu-Gong-Ying 1X
Dang-Gui 3X

QUESTIONS

Professional Formulas

PO Box 2034 Lake Oswego, OR 97035

INDICATIONS

For the temporary relief of mild abdominal discomfort or cramping, bloating, constipation, or diarrhea.*

PURPOSE

*Claims based on traditional homeopathic practice, not accepted medical evidence. Not FDA evaluated.

WARNINGS

Severe or persistent symptoms may be serious. Consult a doctor promptly. Keep out of the reach of children. In case of overdose, get medical help or contact a poison control center right away. If pregnant or breastfeeding, ask a healthcare professional before use.

Keep out of the reach of children.

PREGNANCY OR BREAST FEEDING

If pregnant or breastfeeding, ask a healthcare professional before use.

DIRECTIONS

Place drops under tongue 30 minutes before/after meals. Adults and children 12 years and over: Take 10 drops up to 3 times per day. Consult a physician for use in children under 12 years of age.

OTHER INFORMATION

Tamper resistant. If seal is broken, do not use. After opening, close container tightly and store at room temperature away from heat.

INACTIVE INGREDIENTS

20% ethanol, purified water.

LABEL

Est 1985

Professional Formulas

Complementary Health

Large Intestine Formula

Homeopathic Remedy

2 FL. OZ. (59 mL)